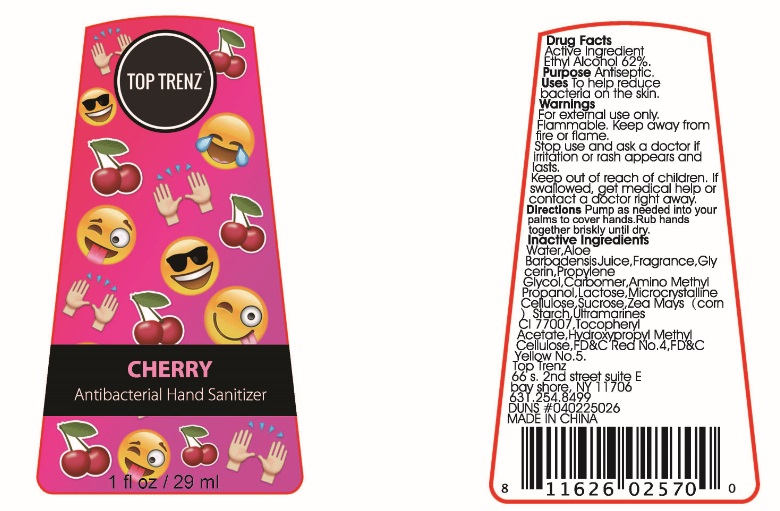 DRUG LABEL: Antibacterial Hand Sanitizer
NDC: 70827-001 | Form: GEL
Manufacturer: Top Trenz
Category: otc | Type: HUMAN OTC DRUG LABEL
Date: 20160718

ACTIVE INGREDIENTS: ALCOHOL 62 mL/100 mL
INACTIVE INGREDIENTS: WATER; ALOE VERA LEAF; GLYCERIN; PROPYLENE GLYCOL; CARBOMER INTERPOLYMER TYPE A (55000 CPS); FD&C YELLOW NO. 5; AMINOMETHYLPROPANOL; LACTOSE; CELLULOSE, MICROCRYSTALLINE; SUCROSE; STARCH, CORN; ULTRAMARINE BLUE; .ALPHA.-TOCOPHEROL ACETATE; HYPROMELLOSES; FD&C RED NO. 4

Active Ingredient: Ethyl Alcohol 62%

Purpose Antiseptic

WARNINGS

Warnings For external use only. Flammable. Keep away from fire or flame.

Stop use and ask a doctor if irritation or rash appears and lasts.

Keep out of reach of children. If swallowed, get medical help or contact a doctor right away.

INACTIVE INGREDIENT

Inactive Ingredients Water, Aloe Barbadensis Leaf Juice, Fragrance, Glycerin, Propylene Glycol, Carbomer, Aminomethyl Propanol, Lactose, Microcrystalline Cellulose, Sucrose, Zea Mays (corn) Starch, Ultramarine Blue CI 77007, Tocopheryl Acetate, Hydroxpropyl Methyl Cellulose, FD&C Red No.4, FD&C Yellow No.5.

INDICATIONS AND USAGE

Uses To help reduce bacteria on the skin.

DOSAGE AND ADMINISTRATION

Directions Pump as needed into your palms to cover hands. Rub hands together briskly unitl dry.